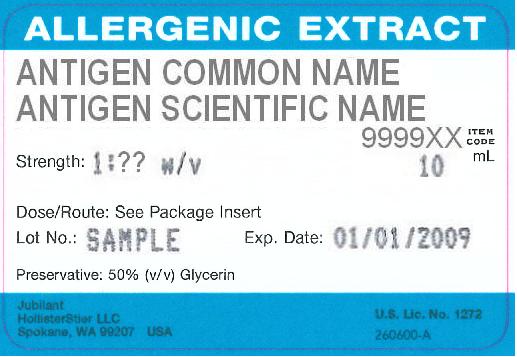 DRUG LABEL: Pollens - Weeds and Garden Plants, Lambs Quarters Chenopodium album
NDC: 65044-1789 | Form: INJECTION, SOLUTION
Manufacturer: Jubilant HollisterStier LLC
Category: other | Type: NON-STANDARDIZED ALLERGENIC LABEL
Date: 20170616

ACTIVE INGREDIENTS: CHENOPODIUM ALBUM POLLEN 0.1 g/1 mL
INACTIVE INGREDIENTS: PHENOL; SODIUM CHLORIDE; SODIUM BICARBONATE

ALLERGENIC EXTRACTS IN BULK VIALS

WARNINGS

This product is intended for use only by licensed medical personnel experienced in administering allergenic extracts and trained to provide immediate emergency treatment in the event of a life-threatening reaction. Allergenic extracts may potentially elicit a severe life-threatening systemic reaction, rarely resulting in death.1

Therefore, emergency measures and personnel trained in their use must be available immediately in the event of such a reaction.
Patients should be instructed to recognize adverse reaction symptoms, be observed in the office for at least 30 minutes after skin testing or treatment, and be cautioned to contact the physician's office if symptoms occur. See ADVERSE REACTION section of this package insert regarding adverse event reporting.
Standardized glycerinated extracts may be more potent than regular extracts and therefore are not directly interchangeable with non-standardized extracts, or other manufacturers' products.
Patients with cardiovascular diseases and/or pulmonary diseases such as symptomatic unstable, steroid dependent asthma, and/or those who are receiving cardiovascular drugs such as beta blockers, may be at higher risk for severe adverse reactions. These patients may also be more refractory to the normal allergy treatment regimen. Patients should be treated only if the benefit of treatment outweighs the risks.1
Patients on beta blockers may be more reactive to allergens given for testing or treatment and may be unresponsive to the usual doses of epinephrine used to treat allergic reactions. 2
This product should never be injected intravenously.
Refer to the WARNINGS, PRECAUTIONS, ADVERSE REACTIONS and OVERDOSE Sections for further discussion.

DESCRIPTION

The allergenic extract in this vial is referred to as a "bulk" extract or stock concentrate since it is designed primarily for the physician equipped to prepare dilutions and mixtures as required. The extract is sterile and intended for subcutaneous injection for immunotherapy and scratch, prick or puncture for diagnosis. Unless specified otherwise, the concentration of extract supplied will in most cases be expressed in weight to volume (e.g., 1:10 or 1:20 w/v) and will be the strongest available. Where mixtures of pollens and non-pollens have been ordered, the mixed extract will be treated as a pollen mixture. To insure maximum potency for the entire dating period, all bulk concentrates will contain 50% volume to volume (v/v) glycerin unless otherwise requested. Dilutions will also be prepared with 50% (v/v) glycerin unless another diluent is specified.
Source materials utilized in allergenic extract products include pollens, molds, animal epidermals, insects, foods and environmental materials.
Pollens are collected using techniques such as waterset or vacuuming, cleaned and purified to greater than 99% single specie pollen (less than 1% foreign particle presence).
Molds are typically grown on synthetic nutrient medias and are derived from the surface growth (mycelia).
Animal source materials are collected from animals deemed to be healthy at the time of collection by a veterinarian or individual trained and certified by a veterinarian. Epidermals include feathers, hair and dander, or the whole epidermal (pelt) as described on product labeling.
Regular process epidermals are extractions of the source material without additional processing, except that certain materials are defatted. AP™ (acetone precipitated) epidermal source materials are derived from the precipitate formed when acetone is added to an aqueous extract. The resulting precipitate is dried, and becomes the source material for the AP™ product.
Insects are collected in whole body form. Extractions take place as whole body or ground insects.
Information on Foods and other Environmental source materials can be obtained by contacting our Customer Service Department.
The following is a brief summary of the six methods of describing allergenic product concentration.

1. Weight to volume (w/v). Weight to volume (w/v) describes the weight of allergenic source material added to a given volume of extracting fluid. A 1:10 w/v extract, e.g., indicates that the solution contains the extractable material from one gram of raw material added to each 10 mL Glycero-Coca's or 10 mL Coca's extracting fluid. The amount and composition of extracted materials will vary with the type of antigen, the extracting fluid, duration of extraction, pH, temperature, and other variables. Pollens are typically extracted at a 1:20 w/v ratio in Glycero-Coca's while Coca's extracts are 1:10 w/v. Epidermal, environmental, regular molds and insect products are typically extracted at 1:10 w/v. AP™ (acetone precipitated) epidermal products are prepared at a 1:50 w/v concentration (i.e., 1 gram of dried precipitate in 50 mL of reconstitution fluid). AP™ Dog Hair-Dander is prepared at 1:100 w/v concentration. (i.e., 1 gram of dried precipitate in 100 mL of reconstitution fluid.)

2. Protein Nitrogen Units per mL (PNU/mL). One protein nitrogen unit represents 0.00001 mg phosphotungstic acid precipitable protein nitrogen dissolved in one mL of antigen extract. The PNU content of extracts of the same antigen may vary according to the method of measuring the PNU. Thus, the PNU content of extracts from different manufacturers is not comparable unless the PNU method is known to be the same and is reproducible from lot to lot. The amount of protein nitrogen extracted from the source material is influenced by such factors as the type of antigen, the extracting fluid, duration of extraction, pH, temperature and other variables. Allergenic materials make up a variable proportion of the total protein of an extract. Most allergenic extracts are assayed for PNU. Specific PNU information is available upon request.

3. Amb a 1. Of the many allergens from Short Ragweed which have been purified and characterized [Amb a 1 3 (also known as Antigen E), Amb a 2 3 (also known as Antigen K), Ra3 4, Ra4 (BPA-R) 5, Ra5 6, Ra6, Ra7, Ra87, and cytochrome C 8], Amb a 1 is considered the most important and has been selected as the basis for standardization. Extracts of Short Ragweed containing Amb a 1 are diffused in agar against standard anti-serum to Amb a 1, and compared to the diffusion of standard Amb a 1 solutions. The amount of Amb a 1 is expressed as units of Amb a 1 per mL of extract. A Short Ragweed pollen extracted at 1:20 (w/v) usually assays within a range of 50,000 to 70,000 PNU/mL and 100 to 300 units of Amb a 1 per mL.
The Amb a 1 concentration of any Short Ragweed extract which is diluted with a diluent or other allergenic extracts is determined by calculation. The resulting Amb a 1 value does not reflect the total potency of the product if Short Ragweed extract is mixed with another allergenic extract.

4. Allergy Units per mL (AU/mL). The potency of extracts labeled in Allergy Units (AU)/mL is determined by in vitro comparison to a reference standard established by the Center for Biologics Evaluation and Research (CBER) of the Food and Drug Administration (FDA).

5. Bioequivalent Allergy Units per mL (BAU/mL). Other standardized allergenic extracts are labeled in Bioequivalent Allergy Units/mL (BAU/mL) based on their comparison (by in vitro assay or major allergen content) to CBER, FDA Reference Preparations. The FDA reference extracts have been assigned Bioequivalent Allergy Units based on the CBER ID50EAL method.9 Briefly, highly sensitive patients are skin tested to the reference preparation using an intradermal technique employing 3-fold extract dilutions. Depending on the dilution which elicits a summation of erythema diameter of 50, Bioequivalent Allergy Units are assigned as follows:

BAU/mL | D50 Range
100,000 | 13.9 - 15.9
10,000 | 10.9 - 12.9
1,000 | 8.8 - 10.8
100 | 6.7 - 8.7

References labeled 10,000 BAU/mL can be diluted one to a half million fold, and references labeled 100,000 BAU/mL can be diluted one to 5 million fold and produce a sum of erythema diameter of 50 mm when Intradermal testing highly reactive subjects.

6. Concentrate. Concentrate label terminology applies to allergenic extract mixtures, where the individual allergens being combined vary in strength or the designation of strength.

e.g. Concentrate
50% Short Ragweed 1:20 w/v
25% Std. Cat Pelt 10,000 BAU/mL
25% Mite D. farinae 10,000 AU/mL

Should the physician choose to calculate the actual strength of each component in the "Concentrate" mixture, the following formulation may be used:

Actual Allergen Strength in Concentrate | = | Allergen Manufacturing Strength | X | % Allergen in Formulation (by volume or parts)

Ingredients: Active ingredients are the allergen(s) noted on the vial label. Preservative is 50% (v/v) glycerin, or 0.4% phenol, as indicated on the vial label. Additional ingredients are 0.5% sodium chloride, and 0.275% sodium bicarbonate.

CLINICAL PHARMACOLOGY

The mechanism by which hyposensitization is achieved is not known completely. It has been shown that repeated injections of appropriate allergenic extracts will ameliorate the intensity of allergic symptoms upon contact with the allergen.11, 12, 13, 14 Clinical studies which address the efficacy of immunotherapy are available. The allergens which have been studied are cat, mite, and some pollen extracts.10, 15, 16, 17, 18, 19

IgE antibodies bound to receptors on mast cell membranes are required for the allergic reaction, and their level is probably related to serum IgE concentrations. Immunotherapy has been associated with decreased levels of IgE, and also with increases in allergen specific IgG "blocking" antibody.
The histamine release response of circulating basophils to a specific allergen is reduced in some patients by immunotherapy, but the mechanism of this change is not clear.
Further study and clarification of the relationships among changes in blocking antibody, reaginic antibody, and mediator-releasing cells, and between these three factors and successful immunotherapy, is needed.

INDICATIONS AND USAGE

20,21,22,23

Allergenic extracts are indicated for use in diagnosis and immunotherapy of patients presenting symptoms of allergy (hay fever, rhinitis, etc.) to specific environmental allergens. The selection of allergenic extracts to be used should be based on a thorough and carefully taken history of hypersensitivity, and confirmed by skin testing.
The use of mixed or unrelated antigens for skin testing is not recommended since, in the case of a positive reaction, it does not indicate which component of the mix is responsible for the reaction, while, in the case of a negative reaction, it fails to indicate whether the individual antigens at full concentration would give a positive reaction. Utilization of such mixes for compounding a treatment may result, in the former case, in administering unnecessary antigens and, in the latter case, in the omission of a needed antigen.
Avoidance of allergens is to be advocated if possible, but cannot always be attained, e.g., allergy to dog dander in kennel owners and employees, dog breeders, research workers, veterinarians, etc.
Allergens to which a patient is extremely sensitive should not be included in treatment mixes with allergens to which there is much less sensitivity, but should be administered separately. This allows individualized and better control of dosage increases, including adjustments in dosage becoming necessary after severe reactions which may occur with the highly reactive allergen.

CONTRAINDICATIONS

There are no known absolute contraindications to immunotherapy. See PRECAUTIONS and WARNINGS.

Patients with cardiovascular diseases and/or pulmonary diseases such as symptomatic unstable, steroid-dependent asthma, and/or those who are receiving cardiovascular drugs such as beta blockers, may be at higher risk for severe adverse reactions. These patients may also be more refractory to the normal allergy treatment regimen. Patients should be treated only if the benefit of treatment outweighs the risks.1
Treat patients only with allergens to which they are allergic by skin test reaction, have a history of symptoms on exposure, and are likely to be exposed to again.
Any injections, including immunotherapy, should be avoided in patients with a bleeding tendency. Patients on beta blockers may be more reactive to allergens given for testing or treatment and may be unresponsive to the usual doses of epinephrine used to treat systemic reactions.2
Since there are differences of opinion concerning the possibility of routine immunizations exacerbating autoimmune diseases, immunotherapy should be given cautiously to patients with other immunologic diseases and only if the risk from exposure is greater than the risk of exacerbating the underlying disorder.

WARNINGS

See WARNINGS box at the beginning of this package insert. See also PRECAUTIONS.

Allergenic extracts must be temporarily withheld from patients or the dose adjusted downward if any of the following conditions exist: (1) severe symptoms of rhinitis and/or asthma; (2) infection or flu accompanied by fever; (3) any evidence of an excessively large local or any generalized reaction during the initial stages of immunotherapy or during maintenance therapy, and/or (4) exposure to excessive amounts of clinically relevant allergen prior to a scheduled injection. Do not administer immunotherapy during a period of symptoms due to exposure. Since the individual components of the extract are those to which the patient is allergic, and to which s/he will be exposed, typical allergic symptoms may follow shortly after the injection, particularly when the antigen load from exposure plus the injected antigen exceeds the patient's antigen tolerance.
THE CONCENTRATE MUST NOT BE INJECTED AT ANY TIME UNLESS TOLERANCE HAS BEEN ESTABLISHED. DILUTE CONCENTRATED EXTRACTS WITH STERILE DILUENT FOR SKIN TESTING AND IMMUNOTHERAPY.
INJECTIONS MUST NEVER BE GIVEN INTRAVENOUSLY. Subcutaneous injection is recommended. Intracutaneous or intramuscular injection may produce large local reactions or be excessively painful.
AFTER INSERTING NEEDLE SUBCUTANEOUSLY, BUT BEFORE INJECTING, ALWAYS WITHDRAW THE PLUNGER SLIGHTLY. IF BLOOD APPEARS IN THE SYRINGE, CHANGE NEEDLE AND GIVE THE INJECTION IN ANOTHER SITE.
IF CHANGING TO A DIFFERENT LOT OF EXTRACT: All extracts lose potency over time, and a fresh extract could have an effective potency that is substantially greater than that of the old extract. Even though it is the same formula and concentration, the first dose from the new vial should not exceed 50% of the previous dose.
IF THE EXTRACT PREVIOUSLY USED WAS FROM ANOTHER MANUFACTURER: Since manufacturing processes and sources of raw materials differ among manufacturers, the interchangeability of extracts from different manufacturers cannot be insured. The starting dose of the extract therefore should be greatly decreased even though the extract is the same formula and dilution. In general, a dose reduction to 50% of the previous product dose should be adequate, but each situation must be evaluated separately considering the patient's history of sensitivity, tolerance of previous injections, and other factors. If the patient tolerates a 50% decrease, the next dose could be raised to the previous dose amount. If the decrease is greater than 50%, the next dose would need to be determined by the allergist, depending on the situation. Dose intervals should not exceed one week when rebuilding dose. See DOSAGE AND ADMINISTRATION.
IF A PROLONGED PERIOD OF TIME HAS ELAPSED SINCE THE LAST INJECTION: Patients may lose tolerance for allergen injections during prolonged periods between doses. The duration of tolerance is an individual characteristic and varies from patient to patient. In general, the longer the lapse in the injection schedule, the greater dose reduction required. If the interval since last dose is over four weeks, perform skin tests to determine starting dose. See DOSAGE AND ADMINISTRATION.
IF THE PREVIOUS EXTRACT WAS OUTDATED: The dating period for allergenic extracts indicates the time that they can be expected to remain potent under refrigerated storage conditions (2° - 8°C). During the storage of extracts, even under ideal conditions, some loss of potency occurs. For this reason, extracts should not be used beyond their expiration date. If a patient has been receiving injections of an outdated extract, s/he may experience excessive local or systemic reactions when changed to a new and possibly more potent extract. In general, the longer the material has been outdated, the greater the dose reduction necessary for the fresh extract.
IF CHANGING FROM ALUM-ADSORBED TO AQUEOUS OR GLYCERINATED EXTRACTS: When the patient was previously receiving alum-adsorbed or alum-precipitated extract, the safest course is to start over as though the patient had not been receiving immunotherapy. See DOSAGE AND ADMINISTRATION and ADVERSE REACTIONS.
IF ANY OTHER CHANGES HAVE BEEN MADE IN THE EXTRACT CONCENTRATE FORMULA: Changes other than those listed above may include situations such as a redistribution of component parts or percentages, a difference in extracting fluid (i.e., change from non-glycerin extracts to 50% glycerin extracts), combining two or more stock concentrates, or any other change. It should be recognized that any change in formula can affect a patient's tolerance of the treatment. The usual 1/2 of the previous dose for a new extract may produce an adverse reaction; extra dilutions are recommended whenever starting a revised formula. The greater the change, the greater the number of dilutions required.
Proper selection of the dose and careful injection should prevent most systemic reactions. It must be remembered that allergenic extracts are highly potent in sensitive individuals, and that systemic reactions of varying degrees of severity may occur, including urticaria, rhinitis, conjunctivitis, wheezing, coughing, angioedema, hypotension, bradycardia, pallor, laryngeal edema, fainting, or even anaphylactic shock and death, as described under ADVERSE REACTIONS. Patients should be informed of this, and the precautions should be discussed prior to immunotherapy. (See PRECAUTIONS.) Severe systemic reactions should be treated as indicated in ADVERSE REACTIONS. Refer to WARNINGS box.

PRECAUTIONS

1. General

The presence of asthmatic signs and symptoms appear to be an indicator for severe reactions following allergy injections. An assessment of airway obstruction either by measurement of peak flow or an alternate procedure may provide a useful indicator as to the advisability of administering an allergy injection.1, 24, 25, 26, 27

Concentrated extracts must not be injected unless tolerance has been established. Concentrated extracts must be diluted prior to use: See DOSAGE and ADMINISTRATION for detailed instructions on the dilution of allergenic extracts.

Any evidence of a local or generalized reaction requires a reduction in dosage during the initial stages of immunotherapy, as well as during maintenance therapy.
Allergenic extracts diluted with sterile Albumin Saline with Phenol (0.4%) may be more potent than extracts diluted with diluents which do not contain stabilizers. When switching from non-stabilized to stabilized diluent, consider weaker initial dilutions for both intradermal testing and immunotherapy.
Sterile solutions, vials, syringes, etc. should be used and aseptic precautions observed in making dilutions.
To avoid cross-contamination, do not use the same needle to withdraw materials from vials of more than one extract, or extract followed by diluent.
A sterile tuberculin syringe graduated in 0.01 mL units and with a needle at least 5/8" long should be used to measure each dose from the appropriate dilution.
Aseptic techniques should always be employed when injections of allergenic extracts are being administered. A separate sterile syringe should be used for each patient to prevent transmission of hepatitis and other infectious agents from one person to another.
Patient reactions to previous injections should be reviewed before each new injection, so that dosage can be adjusted accordingly. See ADVERSE REACTIONS and WARNINGS.
Rarely, a patient is encountered who develops systemic reactions to minute doses of allergen and does not demonstrate increasing tolerance to injections after several months of treatment. If systemic reactions or excessive local responses occur persistently at very small doses, efforts at immunotherapy should be stopped.
PATIENTS SHOULD BE OBSERVED IN THE OFFICE FOR AT LEAST 30 MINUTES AFTER SKIN TESTING AND EACH TREATMENT INJECTION. Most severe reactions will occur within this time period, and rapid treatment measures should be instituted. See ADVERSE REACTIONS for such treatment measures.
In order to avoid darkening and possible precipitation, do not dilute the following extracts with solutions containing phenol: Privet pollen and food extracts of White Potato, Corn, Oat, Rye, and Wheat. Injections of such extracts discolored by reaction with phenol may produce a lasting tattoo-like discoloration of the skin.

2. Information for Patients

Patients should be instructed in the recognition of adverse reactions to immunotherapy, and in particular, to the symptoms of shock. (See WARNINGS box at the beginning of this package insert.) Patients should be made to understand the importance of a 30 minute observation period, and be cautioned to return to the office promptly if symptoms occur after leaving. Patients should be instructed to report any symptoms of exposure to the allergen, so the physician can adjust the dosage appropriately.

3. Drug Interactions

Patients with cardiovascular diseases and/or pulmonary diseases such as symptomatic unstable, steroid-dependent asthma, and/or those who are receiving cardiovascular drugs such as beta blockers, may be at higher risk for severe adverse reactions. These patients may also be more refractory to the normal allergy treatment regimen. Patients should be treated only if the benefit of treatment outweighs the risks.1
Patients on beta blockers may be more reactive to allergens given for testing or treatment and may be unresponsive to the usual doses of epinephrine used to treat allergic reactions.2 (See WARNINGS). Certain medications may lessen the skin test wheal and erythema responses elicited by allergens and histamine for varying time periods. Conventional antihistamines should be discontinued at least 5 days before skin testing. Long acting antihistamines should be discontinued for at least 3 weeks prior to skin testing. 28 Topical steroids should be discontinued at the skin test site for at least 2-3 weeks before skin testing.28, 29
Tricyclic antidepressants such as Doxepin should be withheld for at least 7 days before skin testing. 30 Topical local anesthetics may suppress the flare responses and should be avoided in skin test sites.31

4. Carcinogenesis, Mutagenesis, Impairment of Fertility

Long-term studies in animals have not been conducted with allergenic extracts to determine their potential for carcinogenicity, mutagenicity or impairment of fertility.

5. Pregnancy

Pregnancy Category C. Animal reproduction studies have not been conducted with allergenic extracts. It is also not known whether allergenic extracts can cause fetal harm when administered to a pregnant woman or can affect reproduction capacity. Allergenic extracts should be given to a pregnant woman only if clearly needed. The physician must carefully consider the benefit-to-risk ratio to both patient and fetus, of performing skin testing or continuing immunotherapy during pregnancy. The recommended precautions (See WARNINGS AND PRECAUTIONS) for preventing adverse reactions are especially important in the pregnant patient. Based on the physician's discretion, immunotherapy maintenance doses may be continued during pregnancy if the patient has not experienced adverse side effects. Immunotherapy is generally not initiated during pregnancy due to the risks associated with systemic reactions and their treatment. 33

6. Nursing Mothers

There are no current studies on the secretion of allergenic extract components in human milk or their effect on the nursing infant. Because many drugs are excreted in human milk, caution should be exercised when allergenic extracts are administered to a nursing woman.

7. Pediatric Use

Since dosage for the pediatric population is the same as for adults 34, 35 larger volumes of solution may produce excessive discomfort. Therefore, in order to achieve the total dose required, the volume of the dose may need to be divided into more than one injection per visit.

8. Geriatric Use

The reactions from immunotherapy can be expected to be the same in elderly patients as in younger ones. Elderly patients may be more likely to be on medication that could block the effect of epinephrine which could be used to treat serious reactions, or they could be more sensitive to the cardiovascular side effect of epinephrine because of pre-existing cardiovascular disease. 36

ADVERSE REACTIONS

Physicians administering allergenic extract testing or treatment materials should be experienced in the treatment of severe systemic reactions. See WARNINGS box at the beginning of this package insert.
1. Local Reactions
Some erythema, swelling or pruritus at the site of injection are common, the extent varying with the patient. Such reactions should not be considered significant unless they persist for at least 24 hours. Local reactions (erythema or swelling) which exceed 4-5 cm in diameter are not only uncomfortable, but also indicate the possibility of a systemic reaction if dosage is increased. In such cases the dosage should be reduced to the last level not causing the reaction and maintained at this level for two or three treatments before cautiously increasing again. Large persistent local reactions may be treated by local cold, wet dressings and/or the use of oral antihistamines. They should be considered a warning of possible severe systemic reactions and an indication of the need for temporarily reduced dosages. A mild burning immediately after the injection is to be expected. This usually subsides in 10 to 20 seconds.

2. Systemic Reactions
With careful attention to dosage and administration, systemic reactions occur infrequently, but it cannot be overemphasized that in sensitive individuals, any injection could result in anaphylactic shock. Therefore, it is imperative that physicians administering allergenic extracts understand and be prepared for the treatment of severe reactions.
Most severe systemic reactions will begin within a 30 minute time period, but systemic reactions may occur at any time after skin tests or immunotherapy. Symptoms may range from mild to life-threatening (due to anaphylaxis)as described below.
Other possible systemic reactions which may occur in varying degrees of severity are laryngeal edema, fainting, pallor, bradycardia, hypotension, angioedema, cough, wheezing, conjunctivitis, rhinitis, and urticaria. Adverse reaction frequency data for allergenic extract administration for testing and treatment show that risk is low. 1, 37
If a systemic or anaphylactic reaction does occur, apply a tourniquet above the site of injection and inject 1:1,000 epinephrine-hydrochloride intramuscularly or subcutaneously into the opposite arm. Loosen the tourniquet at least every 10 minutes. Do not obstruct arterial blood flow with the tourniquet.
EPINEPHRINE DOSAGE:
ADULT: 0.3 to 0.5 mL should be injected. Repeat in 5 to 10 minutes if necessary.
PEDIATRIC: The usual initial dose is 0.01 mg (mL) per kg body weight or 0.3 mg (mL) per square meter of body surface area. Suggested dosage for infants to 2 years of age is 0.05 mL to 0.1 mL; for children 2 to 6 years, 0.15 mL; and children 6 to 12 years, 0.2 mL. Single pediatric doses should not exceed 0.3 mg (mL). Doses may be repeated as frequently as every 20 minutes, depending on the severity of the condition and the response of the patient. After administration of epinephrine, profound shock or vasomotor collapse should be treated with intravenous fluids, and possibly vasoactive drugs. Airway patency should be insured. Oxygen should be given by mask. Intravenous antihistamine, inhaled bronchodilators, theophylline and/or adrenal corticosteroids may be used if necessary after adequate epinephrine and circulatory support has been given. Emergency resuscitation measures and personnel trained in their use must be available immediately in the event of a serious systemic or anaphylactic reaction not responsive to the above measures [Ref. J. Allergy and Clinical Immunology, 77(2):p. 271-273, 1986].
Rarely are all of the above measures necessary; the tourniquet and epinephrine usually produce prompt responses. However, the physician should be prepared in advance for all contingencies. Promptness in beginning emergency treatment measures is of utmost importance.
Severe systemic reactions mandate a decrease of at least 50% in the next dose, followed by cautious increases. Repeated systemic reactions, even of a mild nature, are sufficient reason for the cessation of further attempts to increase the reaction-causing dose.

3. Adverse Event Reporting
Report all adverse events to Jubilant HollisterStier LLC, Customer Technical Services Department at 1 (800) 992-1120. A voluntary adverse event reporting system for health professionals is available through the FDA MEDWATCH program. Preprinted forms (FDA Form 3500) are available from the FDA by calling 1 (800) FDA-1088. Completed forms should be mailed to MEDWATCH, 5600 Fisher Lane, Rockville, MD 20852-9787 or Fax to: 1 (800) FDA-0178.

OVERDOSE SECTION

See ADVERSE REACTIONS.

DOSAGE AND ADMINISTRATION

1. General

Parenteral drug products should be inspected visually for particulate matter and discoloration prior to administration, whenever solution and container permit.

Dosage of allergenic extracts is a highly individualized matter and varies according to the degree of sensitivity of the patient, his clinical response, and tolerance to the extract administered during the early phases of an injection regimen.
Allergen extracts should be administered using a sterile syringe with 0.01 mL gradations and a 25-27 gauge x 1/2" to 5/8" needle. The injections are given subcutaneously. The most common sites of injection are the lateral aspect of the upper arm or thigh. Intracutaneous or intramuscular injections may produce large local reactions and may be very painful.
Sterile aqueous diluent containing human serum albumin [Albumin Saline with Phenol (0.4%)] or diluent of 50% glycerin may be used when preparing dilutions of the concentrate for immunotherapy. Dilutions should be made accurately and aseptically, using sterile diluent, vials, syringes, etc. Mix thoroughly and gently by rocking or swirling. Maintain stock solutions and dilutions constantly at 2° - 8°C. To prepare dilutions for intradermal and therapeutic use, make a 1:10 dilution by adding 1.0 mL of the Concentrate to 9.0 mL of sterile aqueous diluent. Subsequent serial dilutions are made in a similar manner.
Following is a suggested schedule for average patients and will be satisfactory in most cases. However, the degree of sensitivity varies in many patients. The size of the dose should be adjusted according to the patient's tolerance and reaction. Decrease the size of the dose if the previous injection resulted in marked local or the slightest general reaction. Another dose should never be given until all reactions resulting from the previous dose have disappeared.
The starting dose should be based on skin tests of the extract to be used for immunotherapy. To determine the starting dose, begin intradermal testing with the most dilute extract preparation. Inject 0.02 mL and read the reaction after 15 minutes. Intradermal testing is continued with increasing concentrations of the extract until a reaction of 10-20 mm erythema (∑ E 0-40 mm) and/or a 5 mm wheal occurs. This concentration at a dose of 0.03 mL then can serve as a starting dose for immunotherapy. Subsequent doses can be increased by 0.03 mL to as high as 0.12 mL increments each time until 0.3 mL is reached, at which time a dilution 10 times as strong can be used, starting with 0.03 mL. Proceed in this way until a tolerance dose is reached or symptoms are controlled. Suggested maintenance dose for a pollen extract is 0.2 mL of the Concentrate, while for a non-pollen extract the maximum suggested dose is 0.5 mL of the Concentrate. Occasionally, higher doses are necessary to relieve symptoms. Special caution is required in administering doses greater than 0.2 mL. The interval between doses is normally 3 to 7 days during dose building regimen.
Normally immunotherapy can be started with a 1:100,000 dilution of extracts labeled in weight/volume. Certain therapeutic mixtures are labeled as Concentrate, (v/v) dilutions of Concentrate, Amb a 1, Allergy units/mL or Bioequivalent Allergy Units/mL. (See DESCRIPTION.) Strength of each antigen in the mixture is indicated in the product labeling. For beginning treatment, use at least a 1,000-fold dilution of the Concentrate extract for non-pollens, and at least a 10,000-fold dilution of the Concentrate extract for pollens.
In some patients, the dosage may be increased more rapidly than recommended above. In seasonal allergies, treatment should be started and the interval between doses regulated so that at least the first twenty doses will have been administered by the time symptoms are expected. Thus, the shorter the interval between the start of immunotherapy and the expected onset of symptoms, the shorter the interval between each dose. Some patients may even tolerate daily doses.
Should symptoms develop before the next injection is scheduled, the interval between doses should be decreased. Should allergic symptoms or local reactions develop shortly after the dose is administered, the size of the dose should be decreased. In seasonal allergies, it is often advisable to decrease the dose to one-half or one-quarter of the maximum dose previously attained if the patient has any seasonal symptoms.
A maintenance dose, the largest dose tolerated by the patient that relieves symptoms without producing undesirable local or general reactions, is recommended for most patients. The upper limits of dosage have not been established; however, doses larger than 0.2 mL of extract may be painful if glycerin is present. The dosage of allergenic extract does not vary significantly with the respiratory allergic disease under treatment. The size of this dose and the interval between doses will vary and can be adjusted as necessary.
The interval between maintenance doses can be increased gradually from one week to 10 days, to two weeks, to three weeks, or even to four weeks, if tolerated. Repeat the doses at a given interval three or four times to check for untoward reactions before further increasing the interval. Protection is lost rapidly if the interval between doses is more than four weeks. (See WARNINGS.)
The usual duration of treatment has not been established. A period of two or three years of injection therapy constitutes an average minimum course of treatment.

2. Pediatric Use

The dose for the pediatric population is the same as for adults.

3. Geriatric Use

The dose for elderly patients is the same as for adult patients under 65.36

HOW SUPPLIED

In 10 mL, 30 mL and 50 mL vials at the w/v, Concentrate, v/v dilution of Concentrate, AU/mL (Standardized Mite Extracts: D. farinae, D. pteronyssinus 10,000 and 30,000 AU/mL; Mite Mixtures: 5,000 AU/mL each species, or 15,000 AU/mL each species), BAU/mL (Standardized Cat Hair and Cat Pelt extracts: 10,000 BAU/mL; Standardized Grass extracts: 10,000 and 100,000 BAU/mL); Amb a 1 units/mL; or PNU/mL ordered by the physician. Please see the current Allergy Product Catalog.

STORAGE AND HANDLING

The expiration date is listed on the container label. To ensure the maximum potency, the extract and its dilutions should be stored at 2° - 8°C, and kept in this temperature range at all times, even during use. Dilutions are less stable than concentrates. If loss of potency is suspected, dilutions should be checked by skin testing with equal v/v dilutions of a freshly prepared dilution on individuals known to be allergic to the specific allergen.

LIMITED WARRANTY

A number of factors beyond our control could reduce the efficacy of this product or even result in an ill effect following its use. These include storage and handling of the product after it leaves our hands, diagnosis, dosage, method of administration and biological differences in individual patients. Because of these factors, it is important that this product be stored properly and that the directions be followed carefully during use. No warranty, express or implied, including any warranty of merchantability or fitness, is made. Representatives of the Company are not authorized to vary the terms or the contents of any printed labeling, including the package insert, for this product except by printed notice from the Company's headquarters. The prescriber and user of this product must accept the terms hereof.

REFERENCES

1. Lockey, R.F., L.M. Benedict, P.C. Turkletaub, S.C. Bukantz. Fatalities from immunotherapy (IT) and skin testing (ST). J. Allergy Clin. Immunol., 79 (4): 660-677, 1987.

2. Jacobs, R.L., G.W. Rake, Jr., et al. Potentiated anaphylaxis in patients with drug-induced beta-adrenergic blockade. J. Allergy Clin. Immunol., 68 (2): 125-127, August 1981.

3. Griffith, I.J., J. Pollock, D.G. Klapper, B.L. Rogers and A.K. Nault. Sequence Polymorphism of Amb a I and Amb a II, the Major Allergens in Ambrosia artemisiifolia (Short Ragweed). Int. Arch. Allergy Apply. Immunol., 96: 296-304, 1991.
4. Underdown, B. J. and L. Goodfriend. Isolation and characterization of an allergen from short ragweed pollen. Biochem. 8 (3): 980-989, 1969.
5. Griffiths, B. W and R. Brunet. Isolation of a basic protein antigen of low ragweed pollen. Can. J. Biochem. 49 (3): 396-400, 1971.
6. Lapkoff, C. B. and L. Goodfriend. Isolation of a low molecular weight ragweed allergen: Ra5. Int. Arch. Allergy Appl. Immunol. 46 (2): 215-229, 1974.
7. Hussain, R. and D. G. March. Characterization and allergenic activity of ragweed allergens Ra6, Ra7, Ra8. J. Allergy Clin. Immunol. 65 (3): 230, abstr. 218, 1980
8. Goodfriend, L., A. M. Choudhury, J. Del Carpio and T. P. King. Cytochrome C: New ragweed pollen allergen. Fed. Proc. 38 (3, part II): 1415, abstr. 6261, 1979.
9. Turkeltaub, P.C., MD, and S.C. Rastogi, PhD. Quantitative intradermal test procedure for evaluation of subject sensitivity to standardized allergenic extracts and for assignment of bioequivalent allergy units to reference preparations using the ID50EAL method. Allergenics Products Testing Laboratory, Center for Biologics Evaluation and Research (CBER), FDA. Revised: November, 1994.
10. Norman, P. S. Postgraduate Course Presentation. An overview of immunotherapy, implications for the future. J. Allergy Clin. Immunol., 65 (2): 87-96, 1980.
11. Lowell, F. C. and W. Franklin. A "double-blind" study of treatment with aqueous allergenic extracts in cases of allergic rhinitis. J. Allergy, 34 (2):165-182, 1963.
12. Lowell, F. C. and W. Franklin. A double-blind study of the effectiveness and specificity of injection therapy in ragweed hay fever. N. Eng. J. Med. 273 (13): 675-679, 1965.
13. Zavazal, V. and A. Stajner. Immunologic changes during specific treatment of the atopic state. II. Acta. Allergol. 25 (1): 11-17, 1970.
14. Reisman, R. E., J. I. Wypych, and E. E. Arbesman. Relationship of immunotherapy, seasonal pollen exposure and clinical response to serum concentrations of total IgE and ragweed-specific IgE. Int. Arch. Allergy Appl. Immunol. 48 (6): 721-730, 1975.
15. Taylor, W. W., J. L. Ohman, F. C. Lowell. Immunotherapy in cat-induced asthma; double-blind trial with evaluation of bronchial responses to cat allergen and histamine. J. Allergy Clin. Immunol., 61 (5): 283-287, 1978.
16. Smith, A. P. Hyposensitization with Dermatophagoides pteronyssinus antigen: Trial in asthma induced by house dust. Br. Med. J., 4: 204-206, 1971.
17. Chapman, M. D., T. A. E. Platts-Mills, M. Gabriel, H. K. Ng, W. G. L. Allen, L. E.Hill, A. J. Nunn. Antibody response following prolonged hyposensitization with Dermatophagoides pteronyssinus extract. Int. Arch. Allergy Appl. Immunol., 61:431-440, 1980.
18. Norman, P. S., W. L. Winkenwerder. Maintenance immunotherapy in ragweed hay fever. J. Allergy, 74: 273-282, 1971.
19. Norman, P. S., W. L. Winkenwerder, L. M. Lichtenstein. Immunotherapy of hay fever with ragweed Antigen E; comparisons with whole pollen extract and placebos. J. Allergy, 42: 93-108, 1968.
20. Middleton, E., C. E. Reed and E. F. Ellis, editors. Allergy Principles and Practice. C. V. Mosby Co., St. Louis, 1978, pp. 877-898.
21. Sheldon, J. M., R. G. Lovell and K. P. Mathews. A Manual of Clinical Allergy, Second Edition. W. B. Saunders. Philadelphia, 1967, pp. 107-112.
22. Sherman, W. B. Hypersensitivity Mechanisms and Management. W. B. Saunders. Philadelphia, 1968, pp. 169-172.
23. Swineford, O. Asthma and Hay Fever. Charles C. Thomas. Springfield, IL, 1971, pp. 148-155.
24. Reid, M.J., R.F. Lockey, P.C. Turkletaub, T.A.E., Platts-Mills. Survey of fatalities from skin testing and immunotherapy. J. 0 Clin. Immunol. 92 (1): 6-15, July 1993.
25. Reid, M.J., G. Gurka. Deaths associated with skin testing and immunotherapy. J. Allergy Clin. Immunol. 97(1) Part 3:231, Abstract 195, January 1996.
26. Thompson, R.A., et al, report of a WHO/IUIS working group. The current status of allergen immunotherapy (hyposensitization). Allergy. 44: 369-379, 1989.
27. Malling, H.J., B. Weeke, et al, The European Academy of Allergology and Clinical Immunology. Position Papers. Allergy. 48 (Supplement 14): 9-82, 1993.
28. Pipkorn, U. Pharmacological influence of anti-allergic medication on In Vivo allergen testing. Allergy. 43: 81-86,1988.
29. Andersson, M. and U. Pipkorn. Inhibition of the dermal immediate allergic reaction through prolonged treatment with topical glucocorticosteroids. J. Allergy Clin. Immunol. 79 (2): 345-349, February 1987.
30. Rao, K.S., et al. Duration of suppressive effect of tricyclic anti-depressants on histamine induced wheal and flare reactions on human skin. J. Allergy Clin. Immunol. 82: 752-757, November 1988.
31. Pipkorn, U., and M. Andersson. Topical dermal anesthesia inhibits the flare but not the wheal response to allergen and histamine in the skin prick test. Clinical Allergy. 17: 307-311, 1987.
32. DuBuske, L.M., C.J. Ling and A.L. Sheffer. Special problems regarding allergen immunotherapy. Immunol. Allergy Clin. North Am. (USA). 12(1): 145-175, 1992.
33. Li, J.T., R.F. Lockey, I.L. Bernstein, J.M. Ortnoy, R.A. Nicklas. Allergen Immunotherapy: A Practice Parameter. Ann. Allergy, Asthma and Immunotherapy 90 (1): 26, 2003.
34. Patterson, R., et al. Allergy Principles and Practice, 2nd ed. E. Middleton, Jr., C. E. Reed, E. F. Ellis, Ed., C. V. Mosby Co., 1983, St. Louis, MO, 1983, Chapter 52
35. Levy, D. A., L. M. Lichtenstein, E. O. Goldstein, and K. Ishizaka. Immunologic and cellular changes accompanying the therapy of pollen allergy. J. Clinical Investigation, 50:360, 1971.
36. Peebles, R.S., Jr., B. Bochner, Howard J. Zeitz, ed. Anaphylaxis in the elderly. Immunology and Allergy Clinics of North America. 13 (3): 627-646, August 1993.
37. Turkeltaub, P.C., MD, and P.J. Gergen, MD. The risk of adverse reactions from percutaneous prick-puncture allergen skin testing, venipuncture, and body measurements: Data from the second National Health and Nutrition Examination Survey 1976-80 (NHANES II). J. Allergy Clin. Immunol. 84(6): 886-890, Dec. 1989.